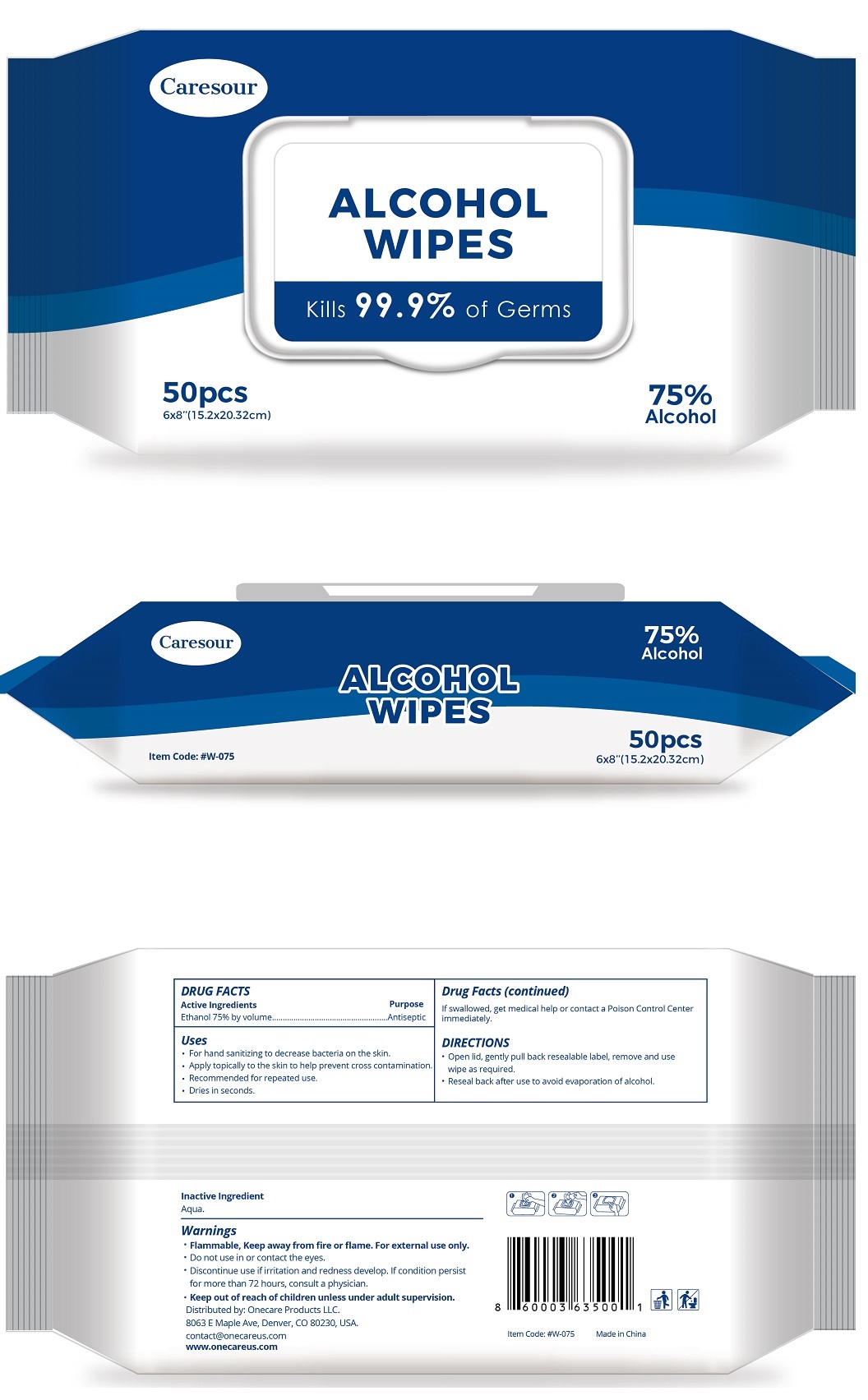 DRUG LABEL: Caresour Alcohol Wipes
NDC: 74614-004 | Form: SWAB
Manufacturer: TAIZHOU BENGTE FURNITURE CO.,LTD
Category: otc | Type: HUMAN OTC DRUG LABEL
Date: 20200416

ACTIVE INGREDIENTS: ALCOHOL 75 g/100 g
INACTIVE INGREDIENTS: WATER

Antibacterial Wipes

Active Ingredient

Ethanol 75% by volume

Purpose

Antiseptic

USE

●For hand sanitizing to decrease bacteria on the skin.
●Apply topically to the skin to help prevent cross contamination.
●Recommended for repeated use.
●Dries in seconds.

Warning

- Flammable, keep away from fire or flame. For external use only.
- Do not use in or contact the eyes.

- Discontiune use if irritaion and redness dvelop. If condition persist for more than 72 hours, consult a physician.

●Keep out of reach of children unless under adult supervision. If swallowed, get medical help or contact a Poison Contrl Center immediately.

Directions

●Open lid, gently pull back resealable label, remove and use wipe as required.
●Reseal back after use to avoid evaporation of alcohol.

Inactive ingredients

Aqua.